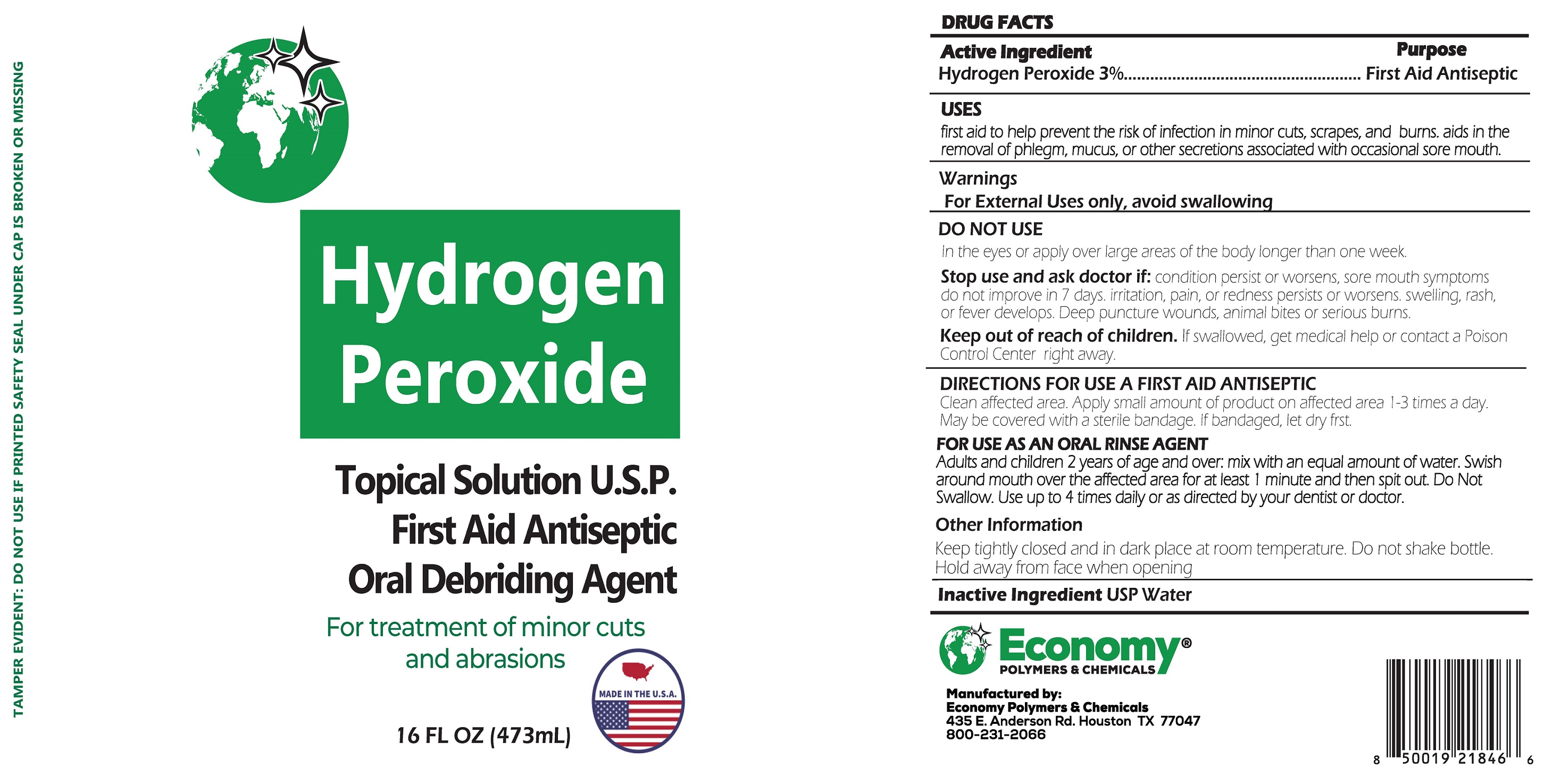 DRUG LABEL: Hydrogen Peroxide Topical Solution U.S.P
NDC: 74830-002 | Form: SOLUTION
Manufacturer: Economy Polymers and Chemicals
Category: otc | Type: HUMAN OTC DRUG LABEL
Date: 20210305

ACTIVE INGREDIENTS: HYDROGEN PEROXIDE 30 mg/1 mL
INACTIVE INGREDIENTS: WATER

Hydrogen Peroxide Topical Solution U.S.P.

Active Ingredient

Hydrogen Peroxide 3%

Purpose

First Aid Antiseptic

USES

first aid to help prevent the risk of infection in minor cuts, scrapes, and burn aids in the removal of phlegm, mucus or other secretions associated with occasional sore mouth.

Warnings

For External Uses only, avoid swallowing

DO NOT USE

in the eyes or apply over large areas of the body longer than one week.

Stop use and ask doctor if:

condition persist or worsens, sore mouth symptoms do not improve in 7 days irritation pain or redenss persists or worsens swelling, rash of fever develops. Deep puncture wounds animal bites or serious burns.

Keep out of reach of children.

If swallowed, get medical help or contact a Poison Control Center right away.

DIRECCTION FOR USE A FIRST AID ANTISEPTIC

Clean affected area. Apply small amount of product on affected area 1-3 times day. May be covered with a sterile bandage. If bandaged let dry first.

FOR USE AS AN ORAL RINSE AGENT

Adults and children 2 years of age and over: mix with an equal amount of water. Swish around mouth over the affected area for at least 1 minute and then spilt out. Do Not Swallow. Use up to 4 times daily or as directed by your dentist or doctor.

Other Information

Keep tightly closed and in dark place at room temperature. Do not shake bottle. Hold away from face when opening

Inactive Ingredient

USP Water